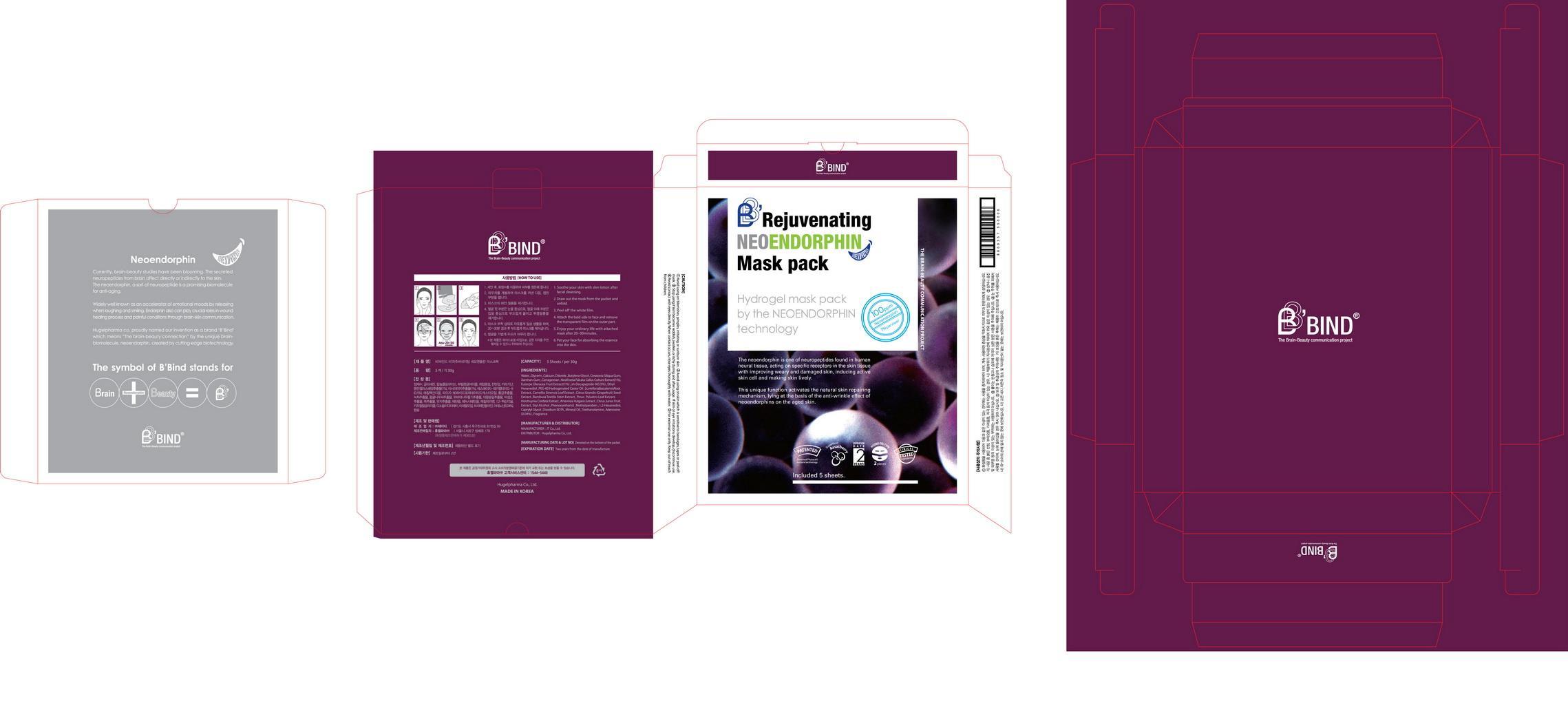 DRUG LABEL: B BIND REJUVENATING NEOENDORPHIN MASK PACK
NDC: 69346-3001 | Form: LIQUID
Manufacturer: HUGEL PHARMA CO.,LTD.
Category: otc | Type: HUMAN OTC DRUG LABEL
Date: 20141101

ACTIVE INGREDIENTS: GLYCERIN 10 g/100 g
INACTIVE INGREDIENTS: BUTYLENE GLYCOL; METHYLPARABEN; ADENOSINE

Drug Facts

ACTIVE INGREDIENT

glycerin

INACTIVE INGREDIENT

water, calcium chloride, butylene glycol, ceratonia siliqua gum, xanthan gum, carrageenan, ethyl hexanediol, etc

PURPOSE

skin moisturizing and repairing

keep out or reach of the children

INDICATIONS AND USAGE

1. Soothe your skin with skin lotion after facial cleansing.
2. Draw out the mask from the packet and unfold.
3. Peel off the film
4. Attach the bald side to face and remove the transparent film on the outer part.
5. Enjoy your ordinary life with attached mask after 20~30 minutes.
6. Pat your face for absorbing the essence into the skin.

Do not use in the following cases(Eczema and scalp wounds)
Due to the use of this druf if rash, irritation, itching and symptopms of hypersnesitivity occur dicontinue use and consult ypur phamacisr or doctor
If in contact with the eyes, wash out thoroughty with water If the symptoms are servere, seek medical advice immediately
This product is for exeternal use only. Do not use for internal use
Storage and handling precautions
If possible, avoid direct sunlight and store in cool and area of low humidity
In order to maintain the quality of the product and avoid misuse
Avoid placing the product near fire and store out in reach of children

DOSAGE AND ADMINISTRATION

for external use only